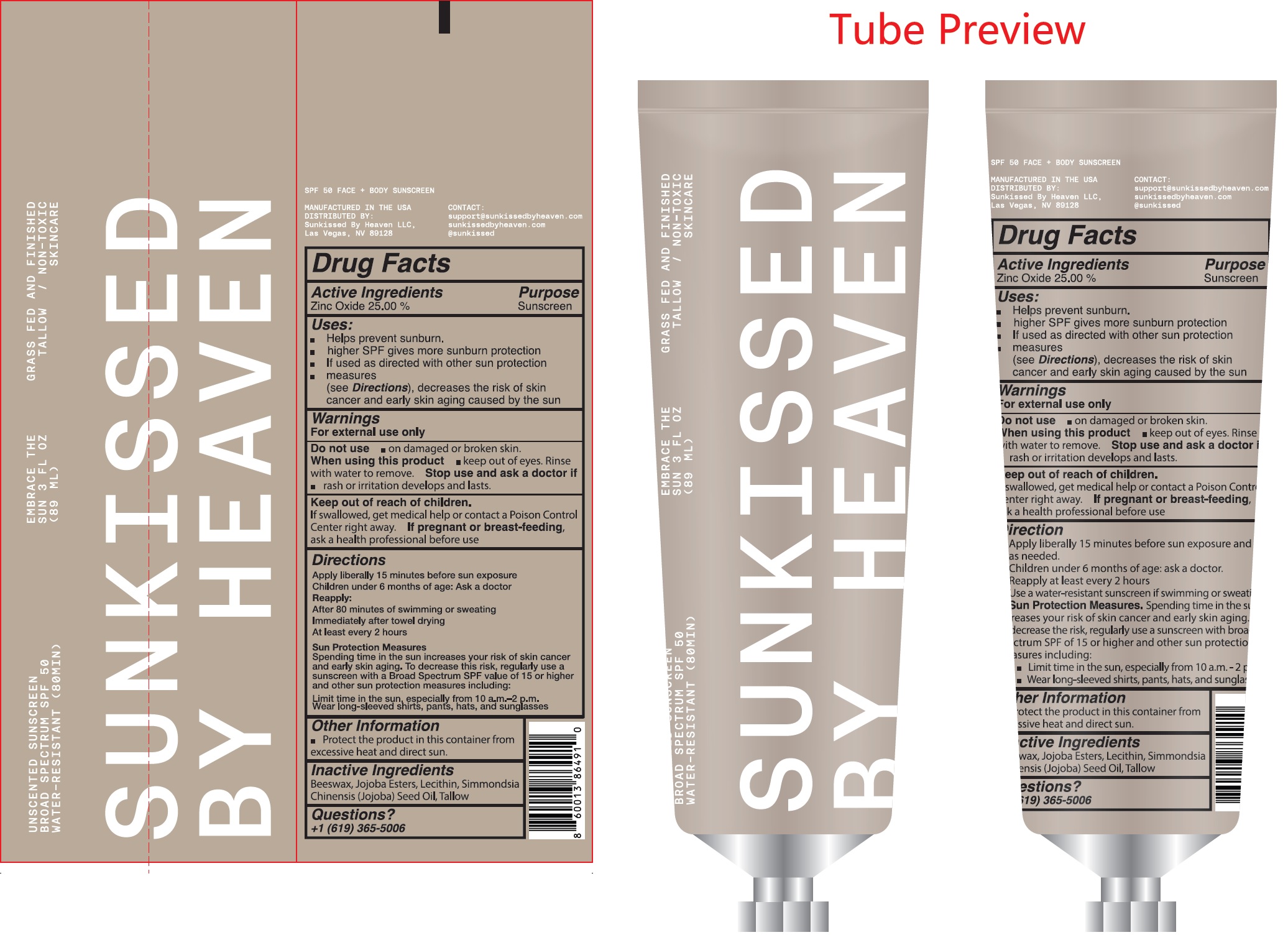 DRUG LABEL: Sunkissed by Heaven Unscented Sunscreen SPF 50
NDC: 87189-910 | Form: OINTMENT
Manufacturer: Sunkissed By Heaven, LLC
Category: otc | Type: HUMAN OTC DRUG LABEL
Date: 20251119

ACTIVE INGREDIENTS: ZINC OXIDE 250 mg/1 mL
INACTIVE INGREDIENTS: BEESWAX; JOJOBA OIL; BEEF TALLOW

Sunkissed by Heaven Unscented Sunscreen SPF 50

Active Ingredients

Zinc Oxide 25.00%

Purpose

Sunscreen

Uses:

- Helps prevent sunburn.
- higher SPF gives more sunburn protection
- If used as directed with other sun protection measures (see Directions), decreases the risk of skin cancer and early skin aging caused by the sun

Warnings

For external use only

Do not use

- on damaged or broken skin.

When using this product

- keep out of eyes. Rinse with water to remove.

Stop use and ask a doctor if

- rash or irritation develops and lasts.

Keep out of reach of children.

If swallowed, get medical help or contact a Poison Control Center right away.

If pregnant or breast-feeding,

ask a health professional before use

Directions

Apply liberally 15 minutes before sun exposure
Children under 6 months of age: Ask a doctor
Reapply:
After 80 minutes of swimming or sweating
Immediately after towel drying
At least every 2 hours
Sun Protection Measures
Spending time in the sun increases your risk of skin cancer and early skin aging. To decrease the risk, regularly use a sunscreen with a Broad Spectrum SPF value of 15 or higher and other sun protection measures including:
Limit time in the sun, especially from 10 a.m-2 p.m.
Wear long-sleeved shirts, pants, hats, & sunglasses

Other Information

- Protect the product in this container from excessive heat and direct sun.

Inactive Ingredients

Beeswax, Jojoba Esters, Lecithin, Simmondsia Chinensis (Jojoba) Seed Oil, Tallow

Questions?

+1 (619) 365-5006